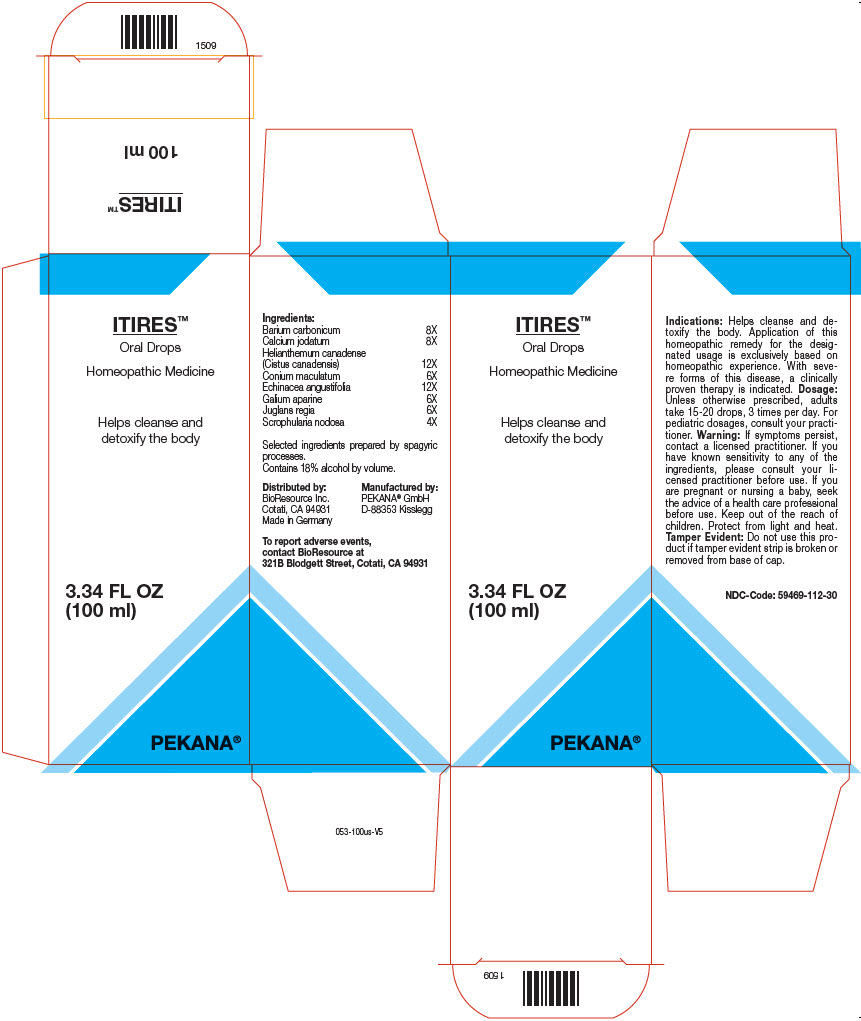 DRUG LABEL: ITIRES
NDC: 59469-112 | Form: SOLUTION/ DROPS
Manufacturer: PEKANA Naturheilmittel GmbH
Category: homeopathic | Type: HUMAN OTC DRUG LABEL
Date: 20221216

ACTIVE INGREDIENTS: Barium Carbonate 8 [hp_X]/50 mL; Calcium Iodide 8 [hp_X]/50 mL; Helianthemum canadense 12 [hp_X]/50 mL; Conium maculatum Flowering Top 6 [hp_X]/50 mL; SCROPHULARIA NODOSA WHOLE 4 [hp_X]/50 mL; Echinacea, unspecified 12 [hp_X]/50 mL; GALIUM APARINE WHOLE 6 [hp_X]/50 mL; Juglans regia Whole 6 [hp_X]/50 mL
INACTIVE INGREDIENTS: Water; Alcohol

ITIRES™

ACTIVE INGREDIENT

Ingredients:
Barium carbonicum | 8X
Calcium jodatum | 8X
Helianthemum canadense (Cistus canadensis) | 12X
Conium maculatum | 6X
Echinacea angustifolia | 12X
Galium aparine | 6X
Juglans regia | 6X
Scrophularia nodosa | 4X

Selected ingredients prepared by spagyric processes.

INACTIVE INGREDIENT

Contains 18% alcohol by volume.

Indications

PURPOSE

Helps cleanse and detoxify the body. Application of this homeopathic remedy for the designated usage is exclusively based on homeopathic experience. With severe forms of this disease, a clinically proven therapy is indicated.

Dosage

Unless otherwise prescribed, adults take 15-20 drops, 3 times per day. For pediatric dosages, consult your practitioner.

Warning

If symptoms persist, contact a licensed practitioner. If you have known sensitivity to any of the ingredients, please consult your licensed practitioner before use. If you are pregnant or nursing a baby, seek the advice of a health care professional before use.

Keep out of the reach of children.

STORAGE AND HANDLING

Protect from light and heat.

Tamper Evident

Do not use this product if tamper evident strip is broken or removed from base of cap.

QUESTIONS

To report adverse events, contact BioResource at 321B Blodgett Street, Cotati, CA 94931

Distributed by:
BioResource Inc.
Cotati, CA 94931

Manufactured by:
PEKANA® GmbH
D-88353 Kisslegg

PRINCIPAL DISPLAY PANEL - 100 ml Bottle Box

ITIRES™
Oral Drops

Homeopathic Medicine

Helps cleanse and
detoxify the body

3.34 FL OZ
(100 ml)

PEKANA®